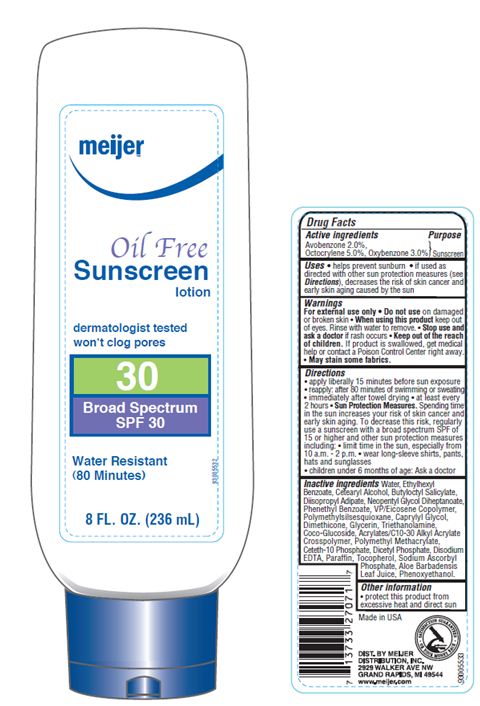 DRUG LABEL: Meijer Oil Free 30
NDC: 41250-012 | Form: LOTION
Manufacturer: Meijer Distribution Inc
Category: otc | Type: HUMAN OTC DRUG LABEL
Date: 20120101

ACTIVE INGREDIENTS: AVOBENZONE 2 mL/100 mL; OCTOCRYLENE 5 mL/100 mL; OXYBENZONE 3 mL/100 mL
INACTIVE INGREDIENTS: WATER; 2-ETHYLHEXYL BENZOATE; CETOSTEARYL ALCOHOL; BUTYLOCTYL SALICYLATE; DIISOPROPYL ADIPATE; NEOPENTYL GLYCOL DIHEPTANOATE; PHENETHYL BENZOATE; POLYMETHYLSILSESQUIOXANE (11 MICRONS); CAPRYLYL GLYCOL; DIMETHICONE; GLYCERIN; TROLAMINE; COCO GLUCOSIDE; CARBOMER INTERPOLYMER TYPE A (55000 CPS); CETETH-10 PHOSPHATE; DIHEXADECYL PHOSPHATE; EDETATE DISODIUM; PARAFFIN; TOCOPHEROL; SODIUM ASCORBYL PHOSPHATE; ALOE VERA LEAF; PHENOXYETHANOL

Drug Facts

Active Ingredients

Avobenzone 2.0%
Octocrylene 5.0%
Oxybenzone 3.0%

Purpose

Sunscreen

Uses

- Helps prevent sunburn
- If used as directed with other sun protection measures (see Directions), decrease the risk of skin cancer and early skin aging caused by the sun.

Warnings

For external use only. Do not useon damaged or broken skin.

When using this product

Keep out of eyes. Rinse with water to remove.

Stop use and ask a doctor

if rash occurs

Keep out of reach of children

If swallowed, get medical help or contact a Poison Control Center right away. May stain some fabrics.

Directions

- apply liberally 15 minutes before sun exposure
- reapply
- after 80 minutes of swimming or sweating
- immediately after towel drying
- at least every 2 hours
- Sun Protection Measures: Spending time in the sun increases your risk of skin cancer and early skin aging. To decrease this risk, regularly use a sunscreen with a broad spectrum SPF of 15 or higher and other sun protection measures including:
- limit time in the sun, especially from 10 a.m. - 2 p.m.
- wear long-sleeve shirts, pants, hats and sunglasses
- children under 6 months of age: Ask a doctor

Inactive ingredients

Water, Ethylhexyl Benzoate, Cetearyl Alcohol, Butyloctyl Salicylate, Diisopropyl Adipate, Neopentyl Glycol Diheptanoate, Phenethyl Benzoate, VP/Eicosene Copolymer, Polymethylsilsesquioxane, Caprylyl Glycol, Dimethicone, Glycerin, Triethanolamine, Coco-Glucoside, Acrylates/C10-30 Alkyl Acrylate Crosspolymer, Polymethyl Methacrylate, Ceteth-10 Phosphate, Dicetyl Phosphate, Disodium EDTA, Paraffin, Tocopherol, Sodium Ascorbyl Phosphate, Aloe Barbadensis Leaf Juice, Phenoxyethanol.

Other Information

protect this product from excessive heat and direct sun